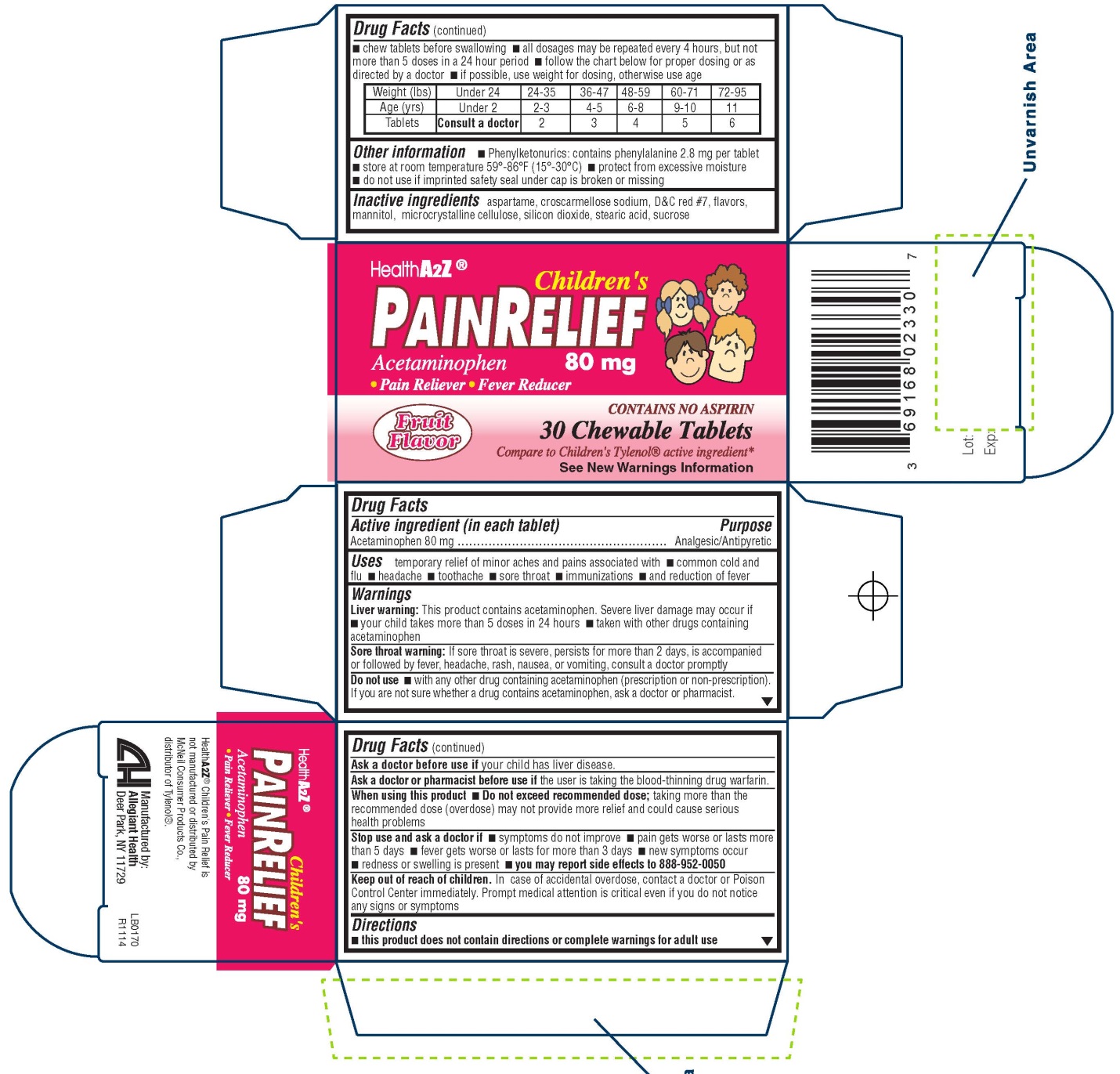 DRUG LABEL: Childrens Pain Relief
NDC: 69168-023 | Form: TABLET
Manufacturer: Allegiant Health
Category: otc | Type: HUMAN OTC DRUG LABEL
Date: 20150303

ACTIVE INGREDIENTS: ACETAMINOPHEN 80 mg/1 1
INACTIVE INGREDIENTS: ASPARTAME; CROSCARMELLOSE SODIUM; D&C RED NO. 7; MANNITOL; CELLULOSE, MICROCRYSTALLINE; SILICON DIOXIDE; STEARIC ACID; SUCROSE

Drug Facts

Active ingredient

Acetaminophen 80 mg

Purpose

Analgesic/Antipyretic

Uses

temporary relief of minor aches and pains associated with common cold and flu headache toothache sore throat immunizations and reduction of fever

Warnings

Liver warning

This product contains acetaminophen. Severe liver damage may occur if your child takes more than 5 doses in 24 hours taken with other drugs containing acetaminophen

Sore throat warning

If sore throat is severe, persists for more than 2 days, is accompanied or followed by fever, headache, rash, nausea, or vomiting, consult a doctor promptly

Do not use

with any other drug containing acetaminophen (prescription or nonprescription). If you are not sure whether a drug contains acetaminophen, ask a doctor or pharmacist

Ask doctor before use if your child has

liver disease

Ask doctor or pharmacist before use if

the user is taking the blood thinning drug warfarin

When using this product

do not exceed recommended dose; taking more than the recommended dose (overdose) may not provide more relief and could cause serious health problems

Stop use and ask a doctor if

symptoms do not improve pain gets worse or lasts more than 5 days fever gets worse or lasts for more than 3 days new symptoms occur redness or swelling is present You may report side effects to 888-952-0050

Keep Out of Reach of Children

In case of accidental overdose, contact a doctor or Poison Control Center immediately. Prompt medical attention is critical even if you do not notice any signs or symptoms

Directions

this product does not contain directions or complete warnings for adult usechew tablets before swallowing all dosages may be repeated every 4 hours, but not more than 5 doses in a 24 hour period follow the chart below for proper dosing or as directed by a doctor if possible, use weight for dosing, otherwise use age

Weight (lbs) | Under 24 | 24-35 | 36-47 | 48-59 | 60-71 | 72-95
Age (yrs) | Under 2 | 2-3 | 4-5 | 6-8 | 9-10 | 11
Tablets | Consult a doctor | 2 | 3 | 4 | 5 | 6

Other information

Phenylketonurics: contains phenylalanine 2.8 mg per tablet store at room temperature protect from excessive moisture do not use if imprinted safety seal under cap is broken or missing

Inactive Ingredients

aspartame, croscarmellose sodium, D&C red #7, flavors, mannitol, microcrystalline cellulose, silicon dioxide, stearic acid, sucrose